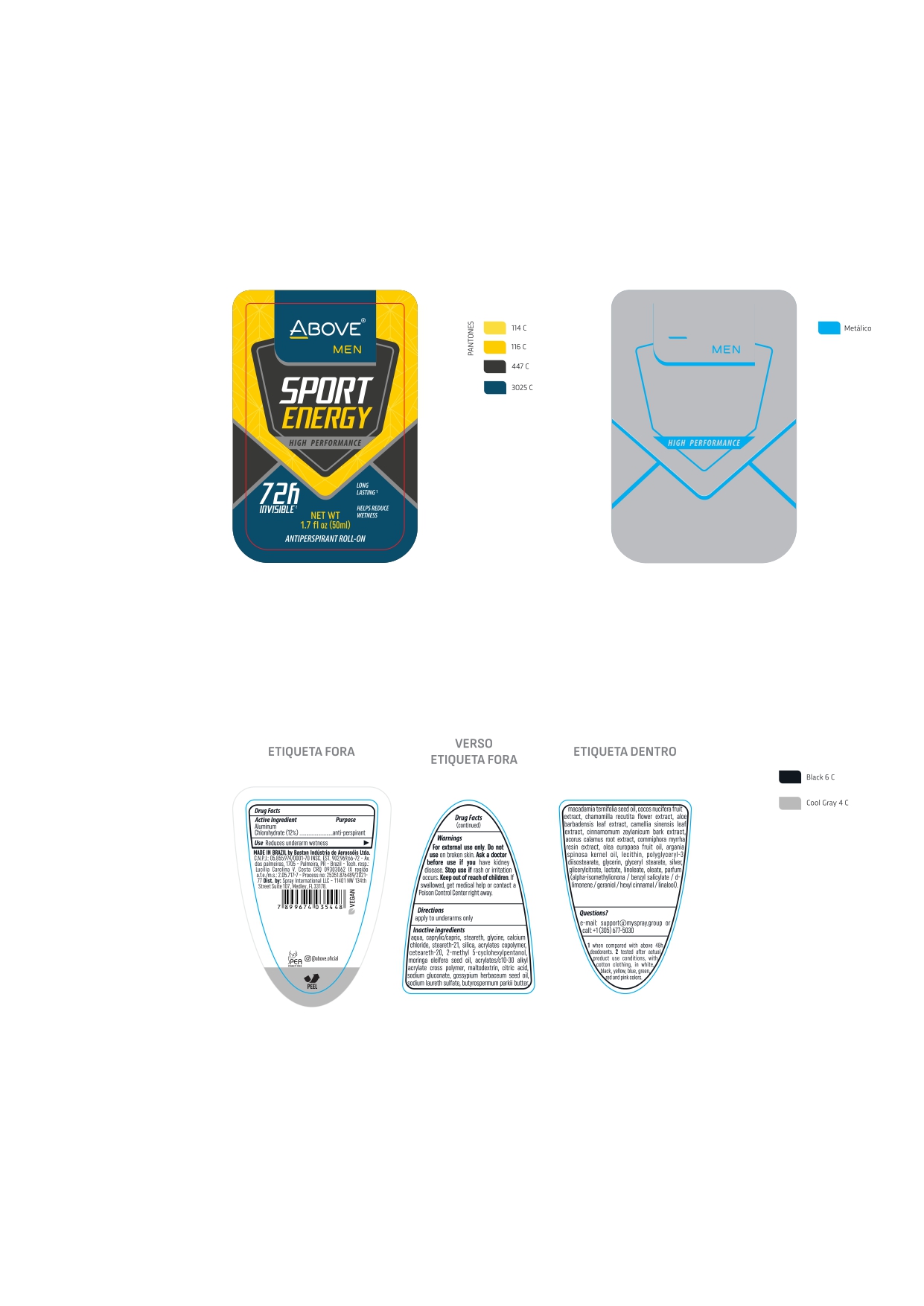 DRUG LABEL: ABOVE MEN SPORT ENERGY
NDC: 73306-1135 | Form: CREAM
Manufacturer: BASTON INDUSTRIA DE AEROSSOIS LTDA
Category: otc | Type: HUMAN OTC DRUG LABEL
Date: 20241226

ACTIVE INGREDIENTS: ALUMINUM CHLOROHYDRATE 50 mg/100 g
INACTIVE INGREDIENTS: MEDIUM-CHAIN TRIGLYCERIDES

ABOVE MEN SPORT ENERGY

ROLL ON DEODORANT ANTIPERSPIRANT

REDUCES UNDEARMS WETNESS

SAC@BASTON.COM.BR OR CALL (305) 677-5030

FOR EXTERNAL USE ONLY. DO NOT USE ON BROKEN SKIN .ASK A DOCTOR BEFORE USE IF YOU HAVE KIDNEY DISEASE.STOP USE IF RASH OR IRRITATION OCCURS. KEEP OUT OF REACH OF CHILDREN IF SWALLOWED,GET MEDICAL HELP OR CONTACT A POISON CONTROL CENTER RIGHT AWAY .

KEEP OUT OF THE CHILDREN

AQUA CAPRYLIC/CAPRIC TRIGLYCERIDE STEARETH 2 GLYCINE CALCIUM CHLORIDE STEARETH-21 PARFUM SILICA ACRYLATES COPOLYMER CETEARETH-20 2-METHYL 5-CYCLOHEXYLPENTANOL MORINGA OLEIFERA SEED OIL ACRYLATES / C10-30 ALKYL ACRYLATE CROSS POLYMER MALTODEXTRIN CITRIC ACID SODIUM GLUCONATE GOSSYPIUM HERBACEUM SEED OIL SODIUM LAURETH SULFATE BUTYROSPERMUM PARKII BUTTER MACADAMIA TERNIFOLIA SEED OIL COCOS NUCIFERA FRUIT EXTRACT CHAMOMILLA RECUTITA FLOWER EXTRACT ALOE BARBADENSIS LEAF EXTRACT CAMELLIA SINENSIS LEAF EXTRACT CINNAMOMUM ZEYLANICUM BARK EXTRACT ACORUS CALAMUS ROOT EXTRACT COMMIPHORA MYRRHA RESIN EXTRACT OLEA EUROPAEA FRUIT OIL ARGANIA SPINOSA KERNEL OIL LECITHIN POLYGLYCERYL-3 DIISOSTEARATE GLYCERIN GLYCERYL STEARATE SILVER GLICERYLCITRATE / LACTATE / LINOLEATE / OLEATE

AQUA
CAPRYLIC/CAPRIC TRIGLYCERIDE
STEARETH 2
GLYCINE
CALCIUM CHLORIDE
STEARETH-21
PARFUM
SILICA
ACRYLATES COPOLYMER
CETEARETH-20
2-METHYL 5-CYCLOHEXYLPENTANOL
MORINGA OLEIFERA SEED OIL
ACRYLATES / C10-30 ALKYL ACRYLATE CROSS POLYMER
MALTODEXTRIN
CITRIC ACID
SODIUM GLUCONATE
GOSSYPIUM HERBACEUM SEED OIL
SODIUM LAURETH SULFATE
BUTYROSPERMUM PARKII BUTTER
MACADAMIA TERNIFOLIA SEED OIL
COCOS NUCIFERA FRUIT EXTRACT
CHAMOMILLA RECUTITA FLOWER EXTRACT
ALOE BARBADENSIS LEAF EXTRACT
CAMELLIA SINENSIS LEAF EXTRACT
CINNAMOMUM ZEYLANICUM BARK EXTRACT
ACORUS CALAMUS ROOT EXTRACT
COMMIPHORA MYRRHA RESIN EXTRACT
OLEA EUROPAEA FRUIT OIL
ARGANIA SPINOSA KERNEL OIL
LECITHIN
POLYGLYCERYL-3 DIISOSTEARATE
GLYCERIN
GLYCERYL STEARATE
SILVER
GLICERYLCITRATE / LACTATE / LINOLEATE / OLEATE